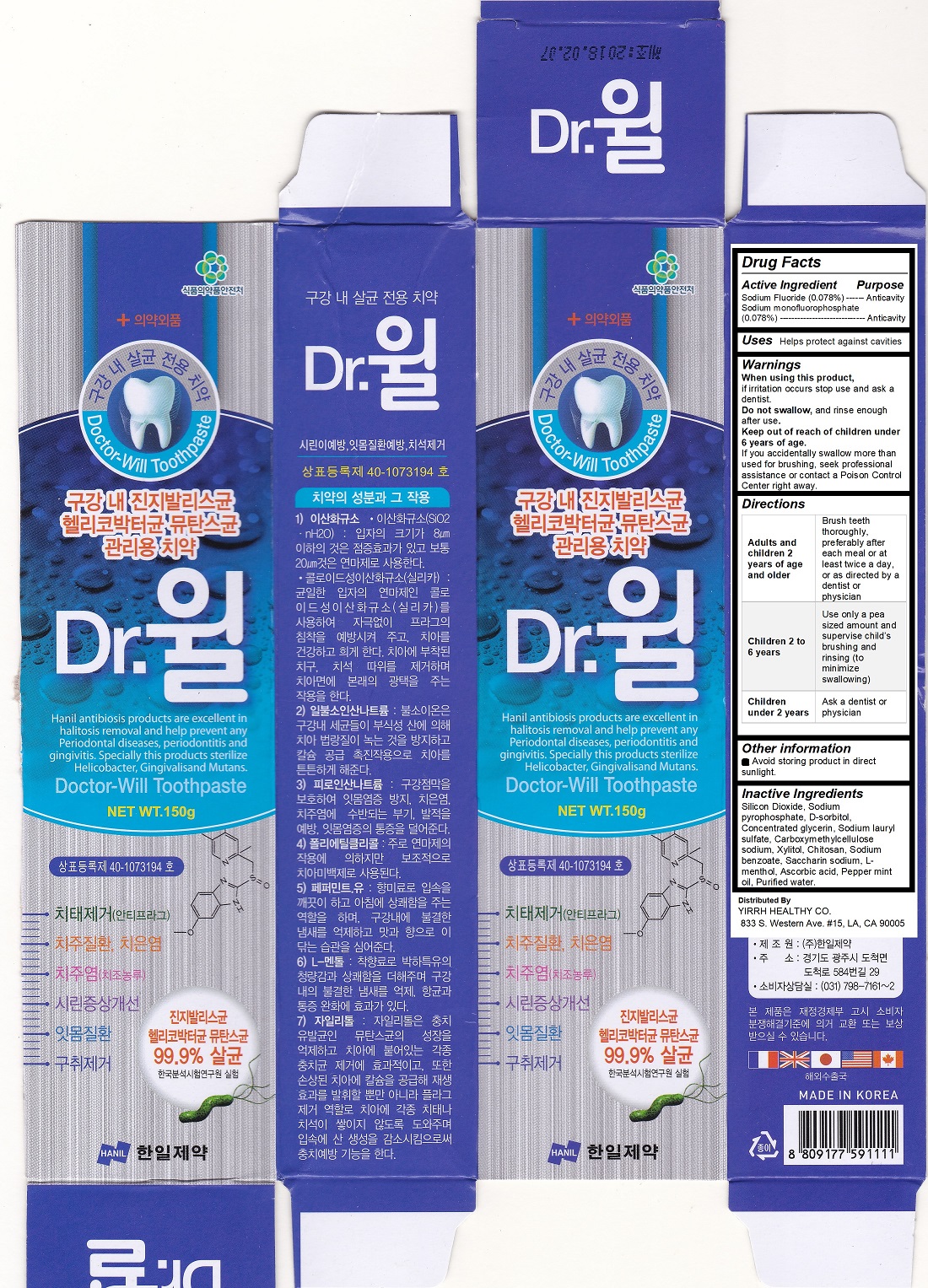 DRUG LABEL: Doctor Will
NDC: 72531-100 | Form: PASTE, DENTIFRICE
Manufacturer: YIRRH HEALTHY LIVING COMPANY
Category: otc | Type: HUMAN OTC DRUG LABEL
Date: 20181001

ACTIVE INGREDIENTS: SODIUM MONOFLUOROPHOSPHATE 0.05 g/150 g; SODIUM FLUORIDE 0.05 g/150 g
INACTIVE INGREDIENTS: SORBITOL

Doctor Will Toothpaste

active ingredient

Sodium Fluoride (0.078%) ------ Anticavity

Sodium monofluorophosphate

(0.078%) ----------------------------- Anticavity

Keep out of reach of children under 6 years of age.

If you accidentally swallow more than used for brushing, seek professional assistance or contact a Poison Control Center right away.

Purpose

Anticavity

Uses

Helps protect against cavities

Warnings

When using this product,

if irritation occurs stop use and ask a dentist.

Do not swallow, and rinse enough after use.

Keep out of reach of children under 6 years of age.

If you accidentally swallow more than used for brushing, seek professional assistance or contact a Poison Control Center right away.

Directions

Adults and children 2 years of age and older

Brush teeth thoroughly, preferably after each meal or at least twice a day, or as directed by a dentist or physician.

Children 2 to 6 years

Use only a pea sized amount and supervise child’s brushing and rinsing (to minimize swallowing).

Children under 2 years

Ask a dentist or physician

Inactive Ingredients

Silicon Dioxide, Sodium pyrophosphate, D-sorbitol, Concentrated glycerin, Sodium lauryl sulfate, Carboxymethylcellulose sodium, Xylitol, Chitosan, Sodium benzoate, Saccharin sodium, L-menthol, Ascorbic acid, Pepper mint oil, Purified water.